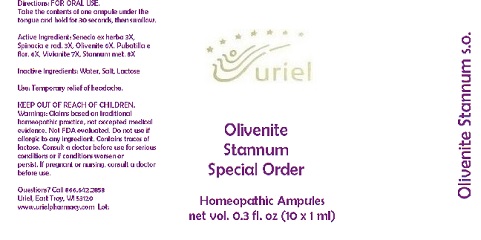 DRUG LABEL: Olivenite Stannum Special Order
NDC: 48951-7086 | Form: LIQUID
Manufacturer: Uriel Pharmacy Inc.
Category: homeopathic | Type: HUMAN OTC DRUG LABEL
Date: 20170803

ACTIVE INGREDIENTS: JACOBAEA VULGARIS 3 [hp_X]/1 mL; SPINACIA OLERACEA ROOT 3 [hp_X]/1 mL; COPPER ARSENATE 6 [hp_X]/1 mL; PULSATILLA VULGARIS 6 [hp_X]/1 mL; FERROSOFERRIC PHOSPHATE 7 [hp_X]/1 mL; TIN 8 [hp_X]/1 mL
INACTIVE INGREDIENTS: WATER; SODIUM CHLORIDE; LACTOSE

Olivenite Stannum Special Order

INDICATIONS AND USAGE

Directions: FOR ORAL USE.

DOSAGE AND ADMINISTRATION

Take the contents of one ampule under the tongue and hold for 30 seconds, then swallow.

Active Ingredient: Senecio ex herba 3X, Spinacia e rad. 3X, Olivenite 6X, Pulsatilla e flor. 6X, Vivianite 7X, Stannum met. 8X

Inactive Ingredients: Water, Salt, Lactose

PURPOSE

Use: Temporary relief of headache.

KEEP OUT OF REACH OF CHILDREN.

WARNINGS

Warnings: Claims based on traditional homeopathic practice, not accepted medical evidence. Not FDA evaluated. Do not use if allergic to any ingredient. Contains traces of lactose. Consult a doctor before use for serious conditions or if conditions worsen or
persist. If pregnant or nursing, consult a doctor before use.

QUESTIONS

Questions? Call 866.642.2858 Uriel, East Troy, WI 53120 www.urielpharmacy.com